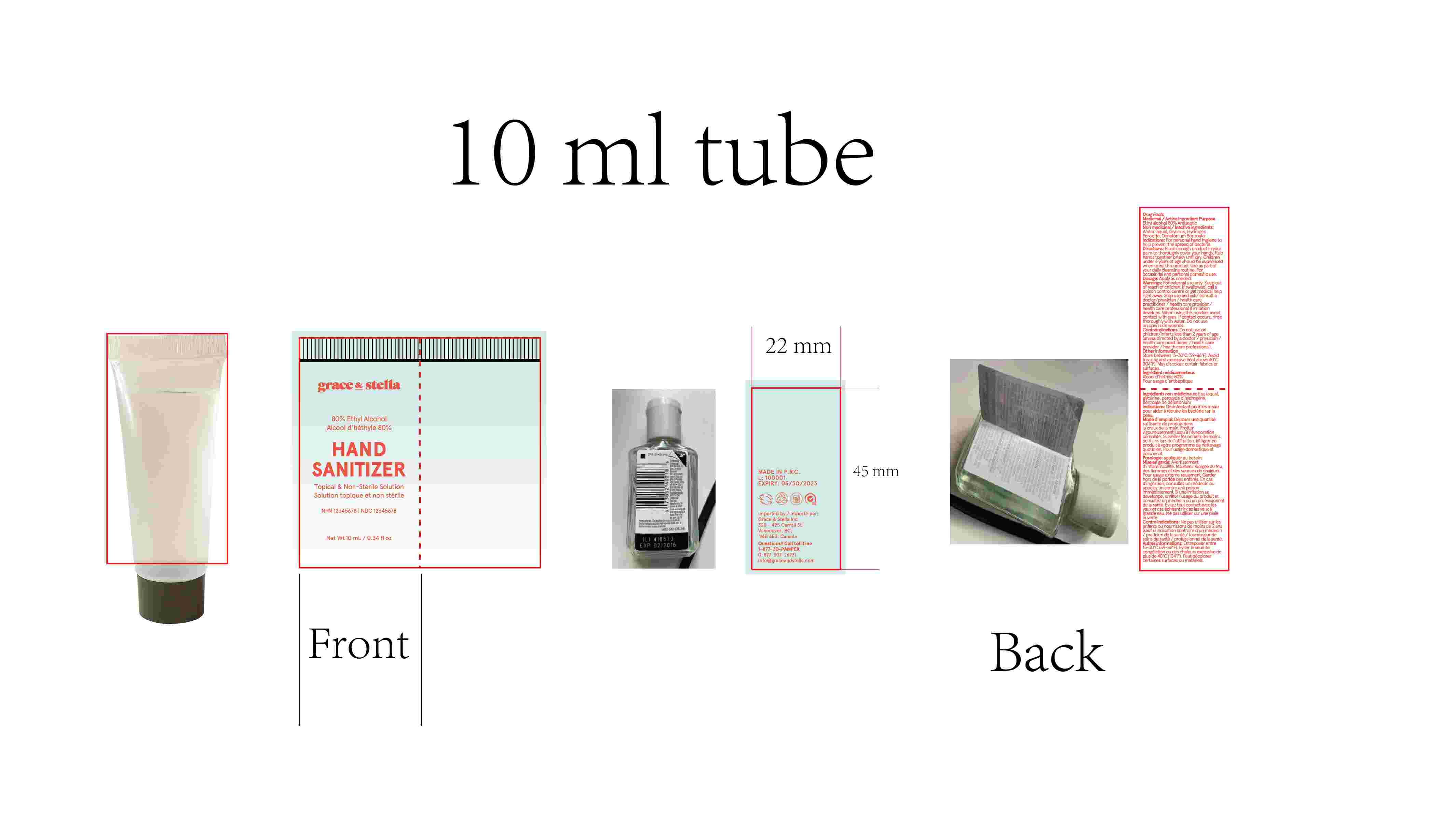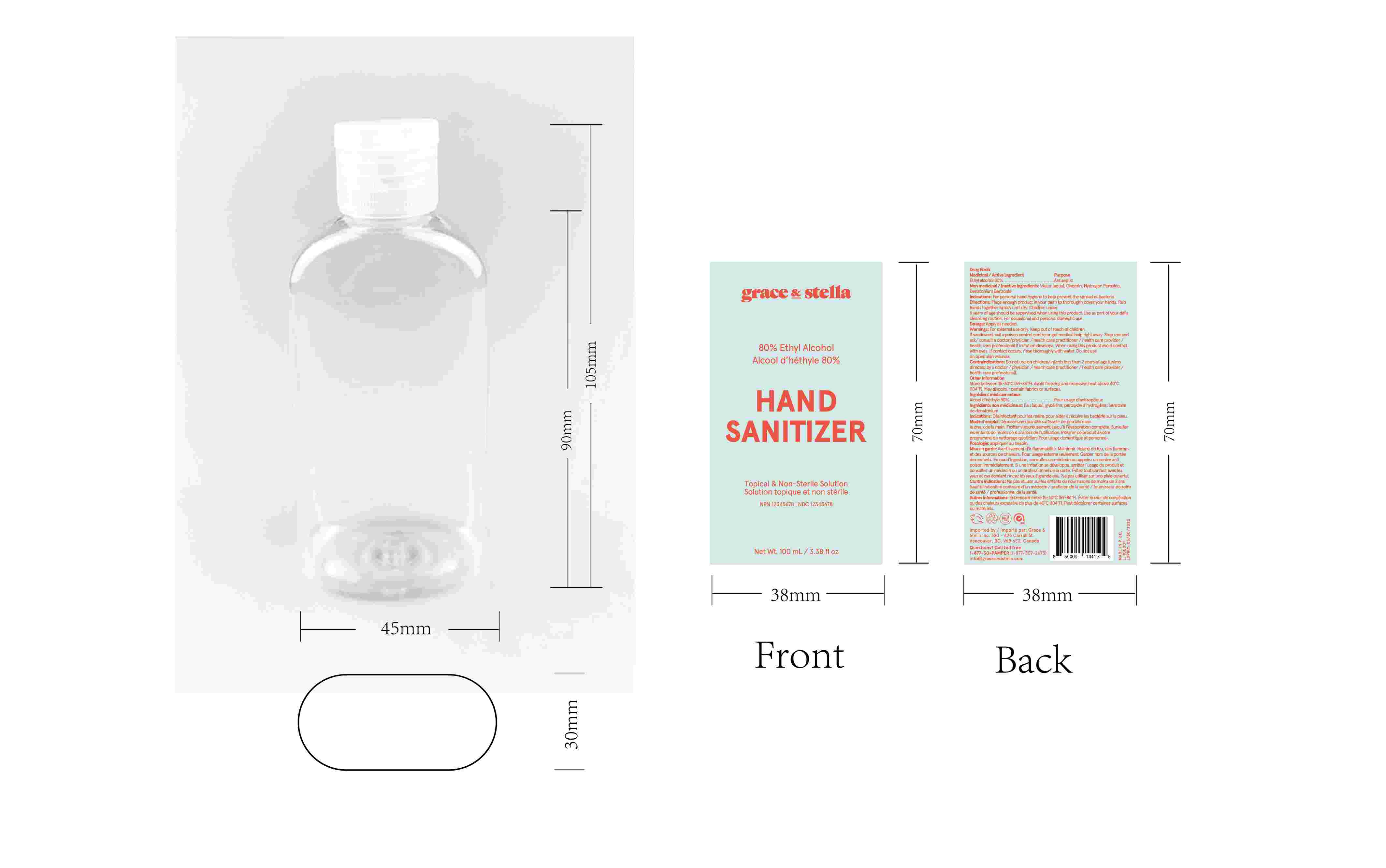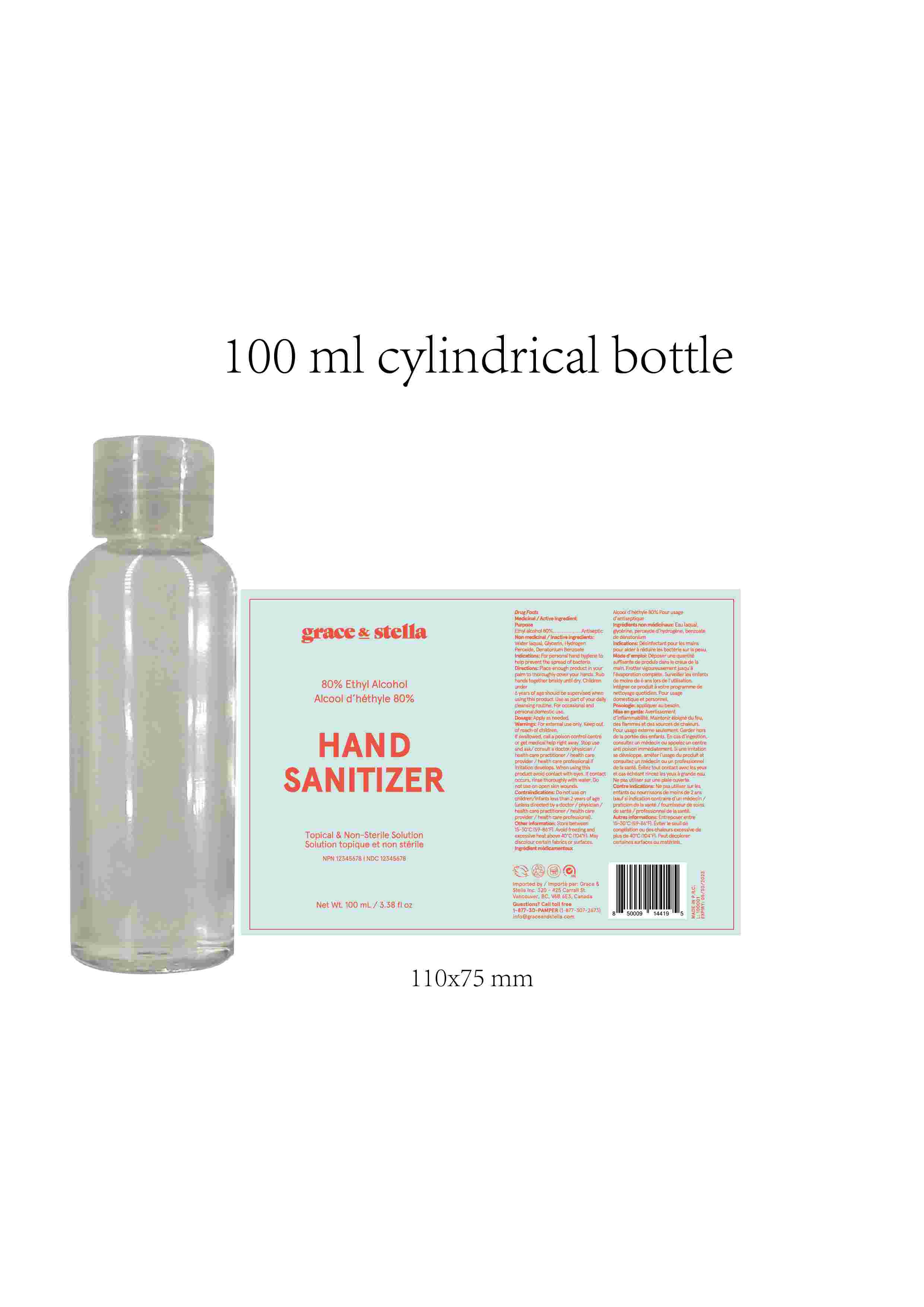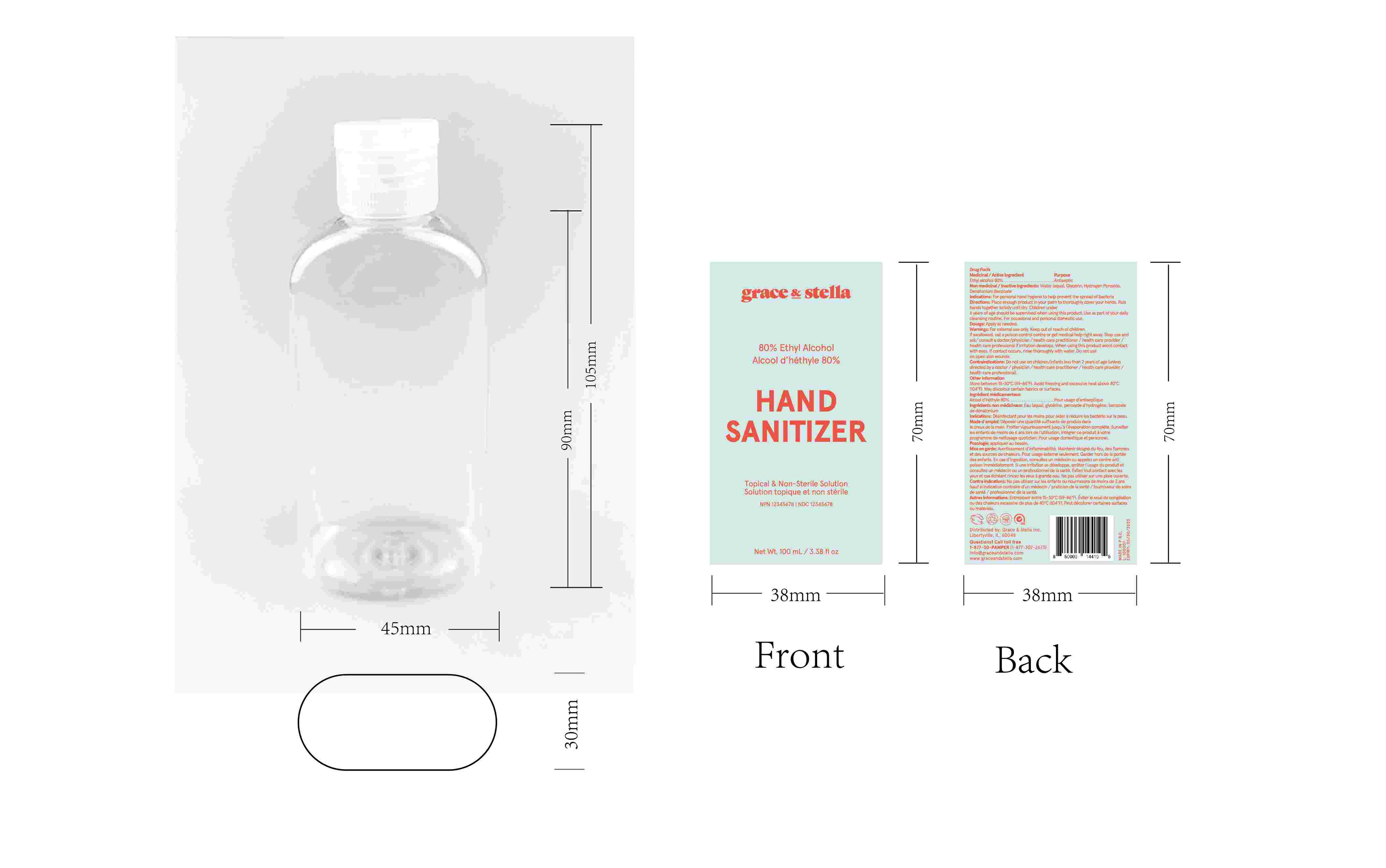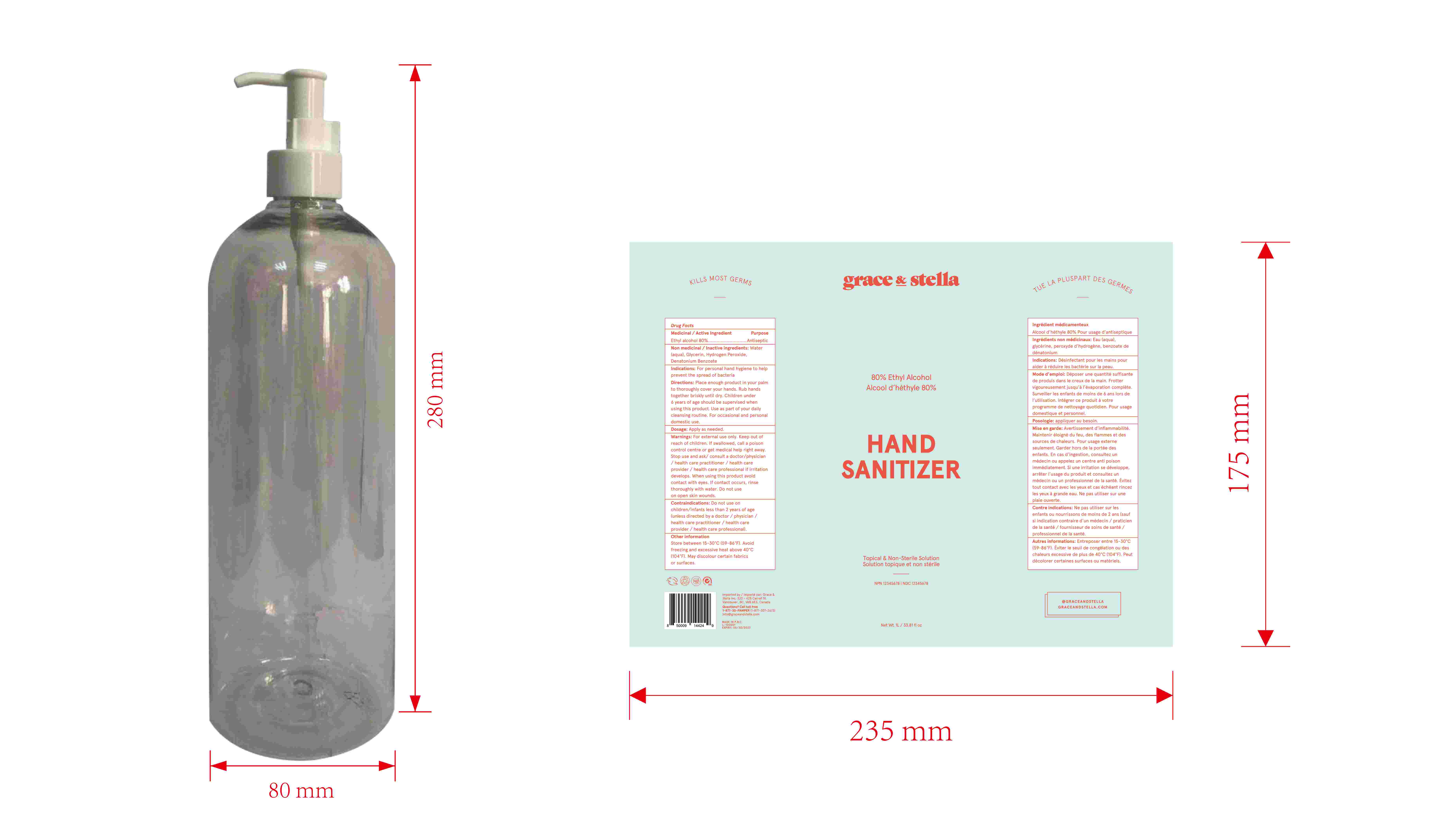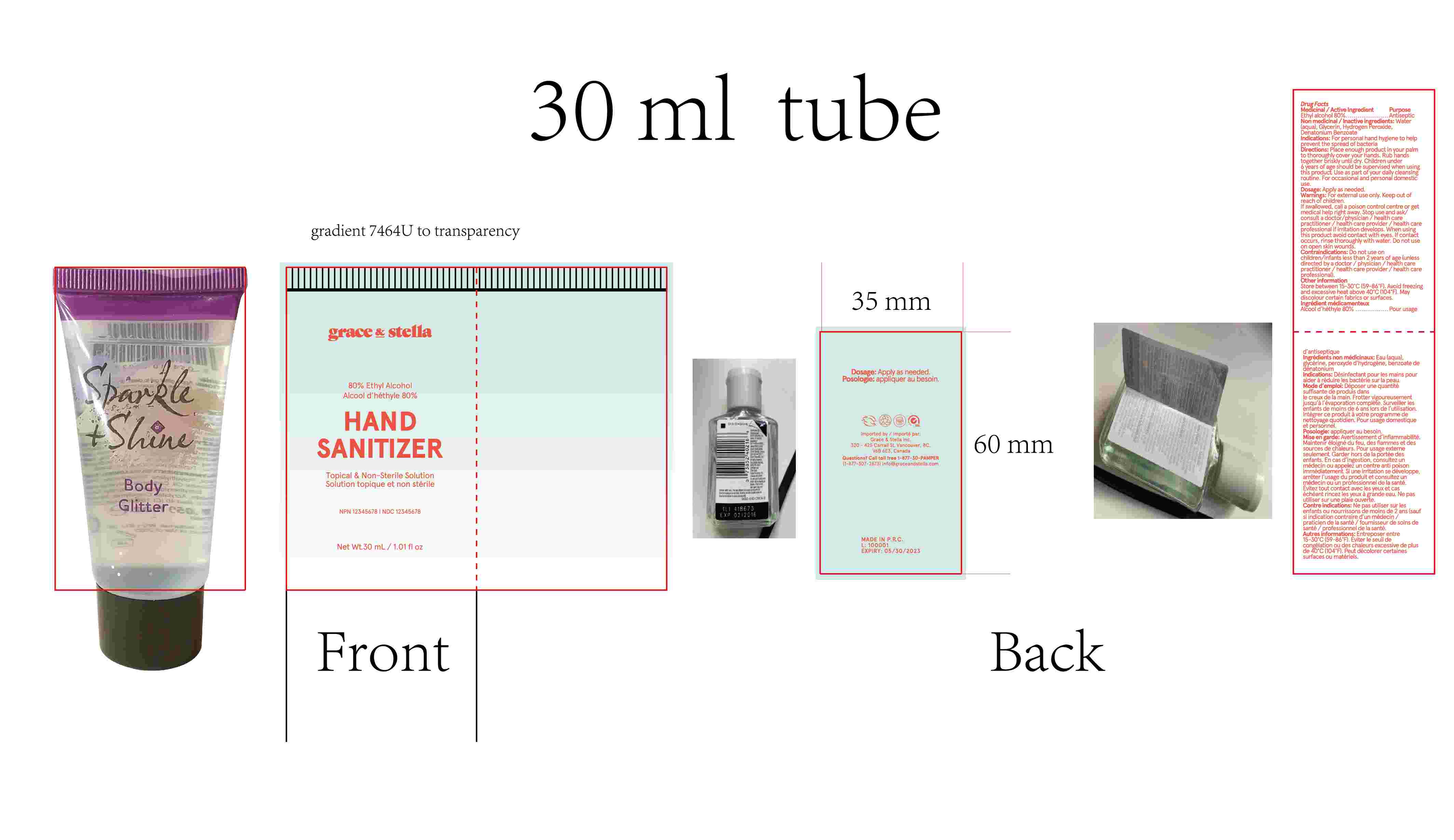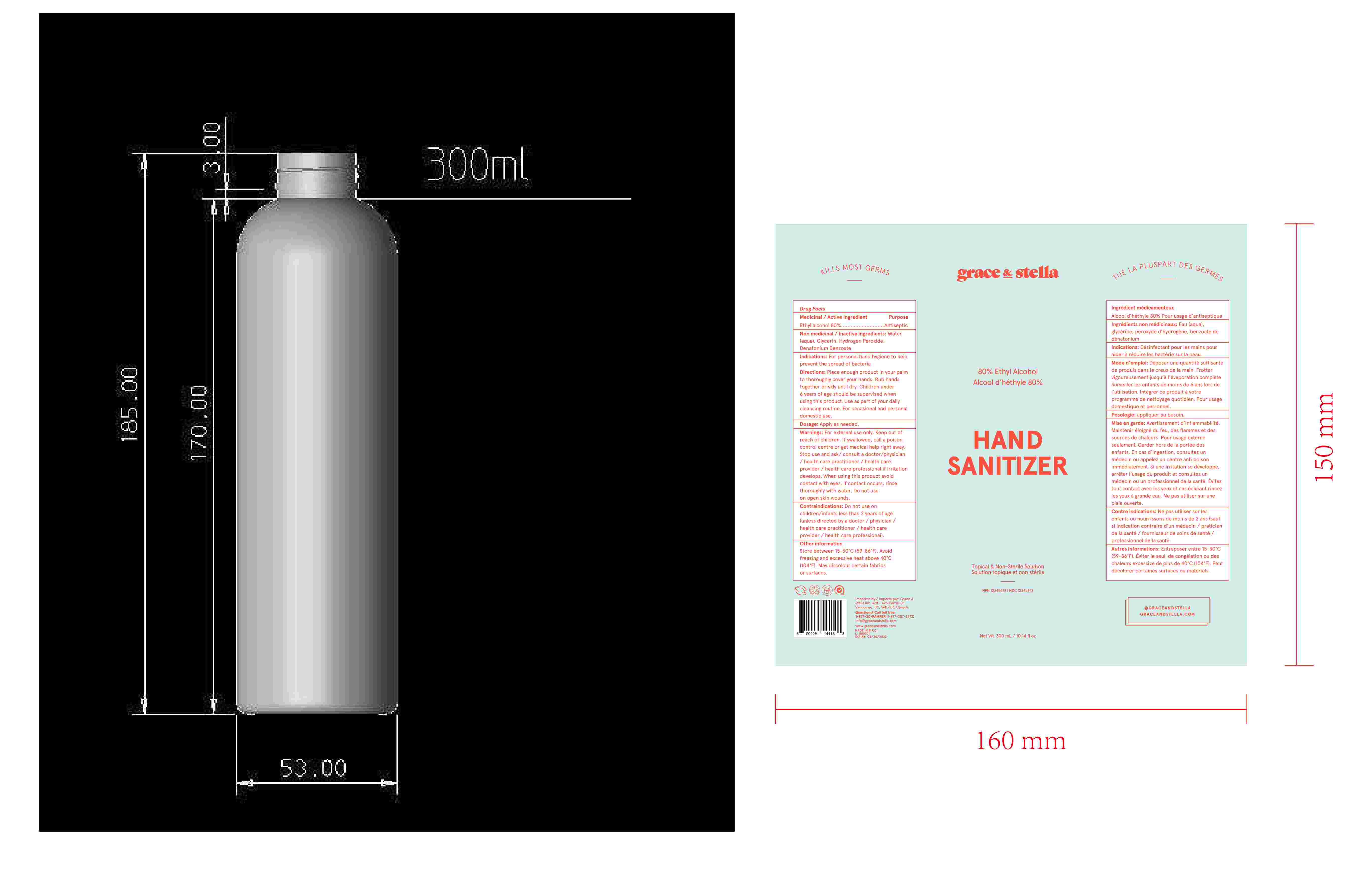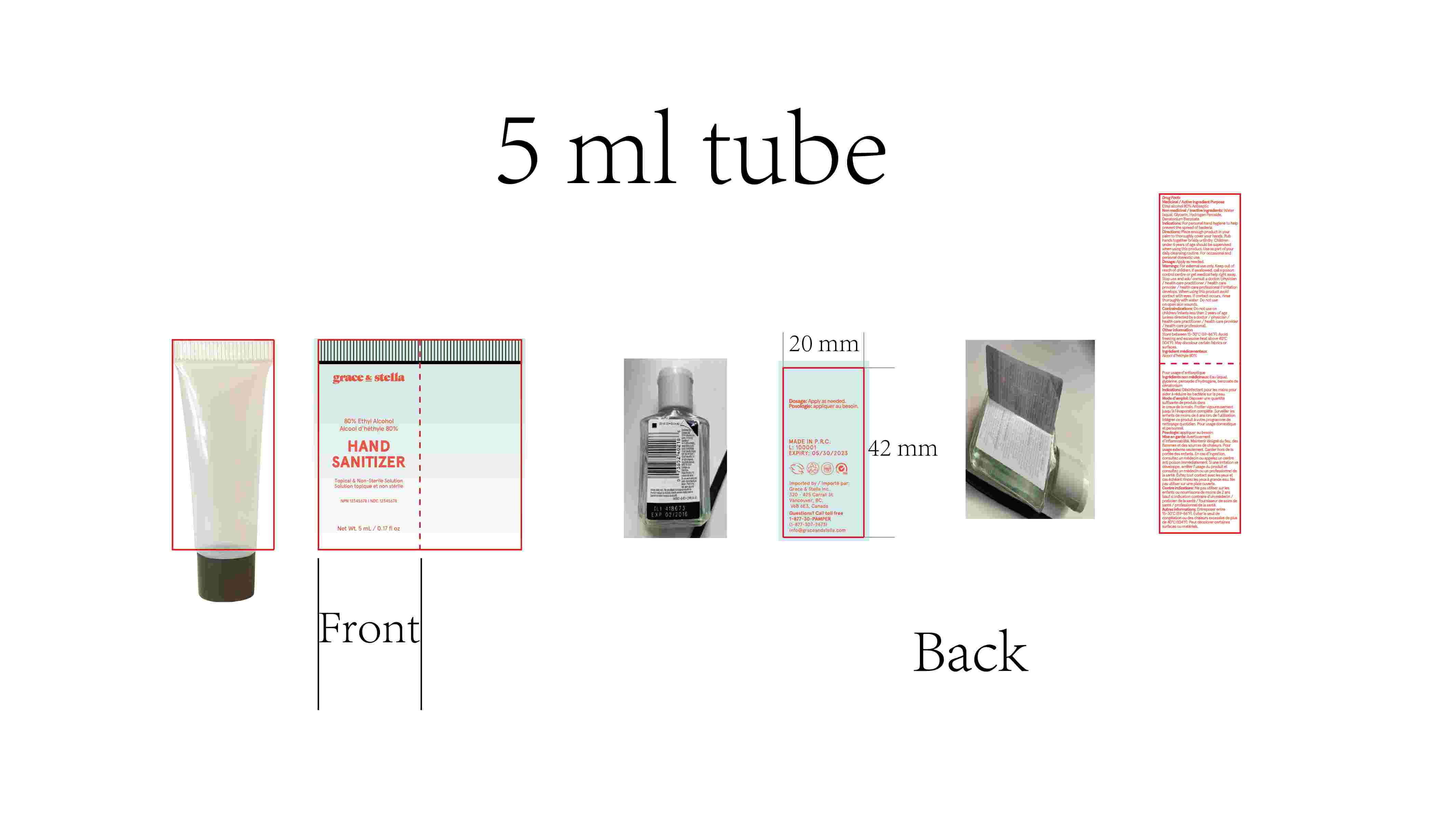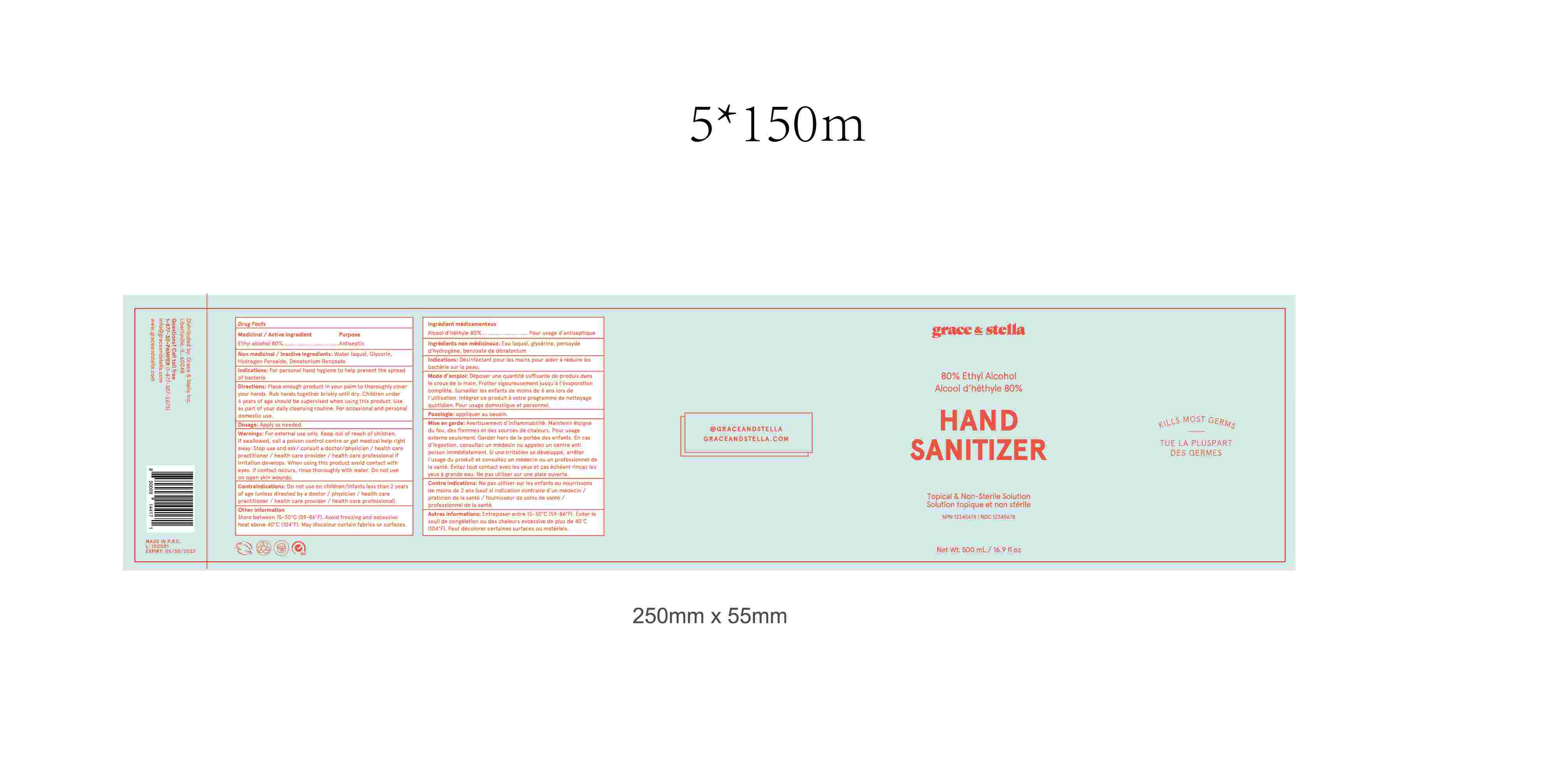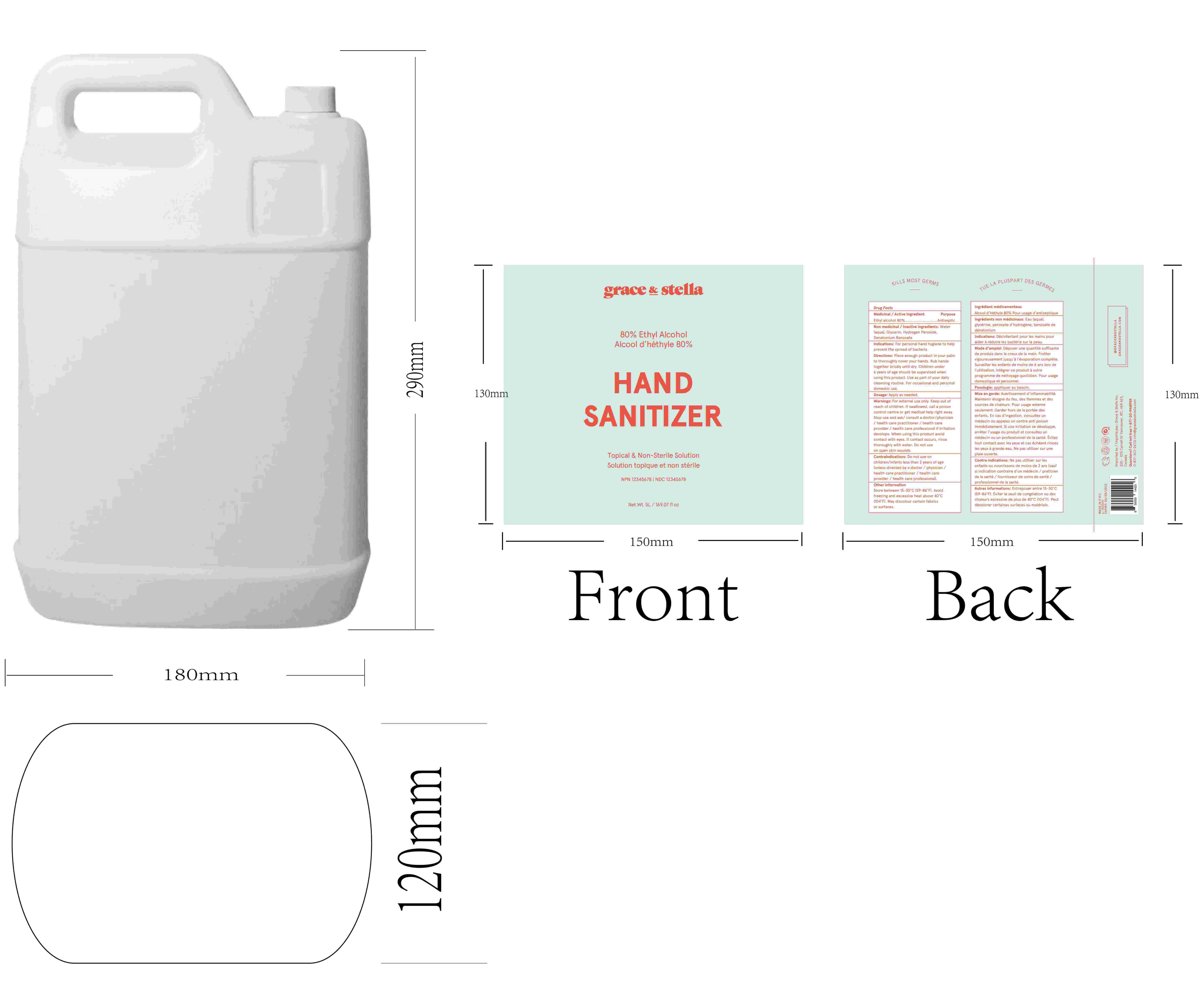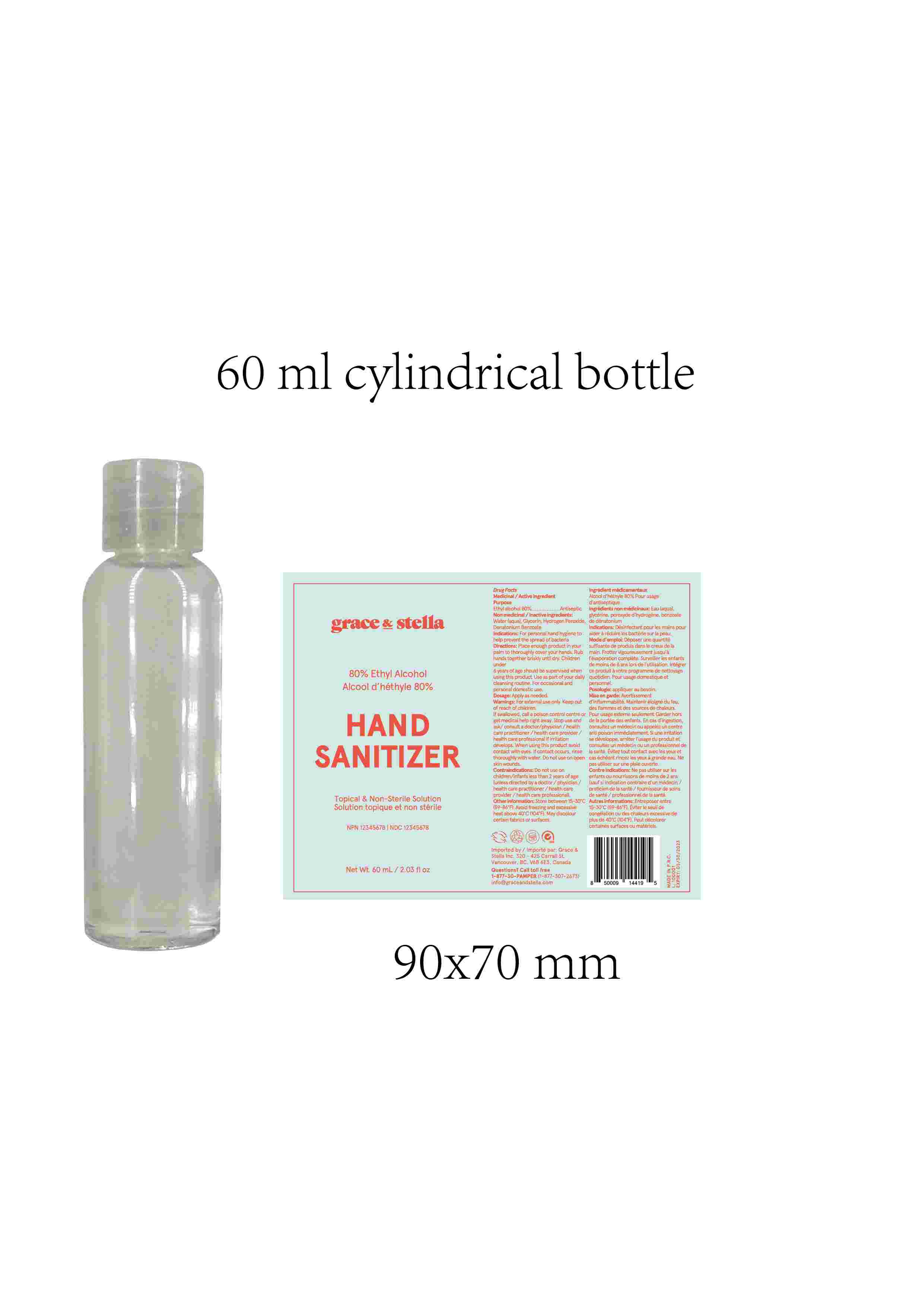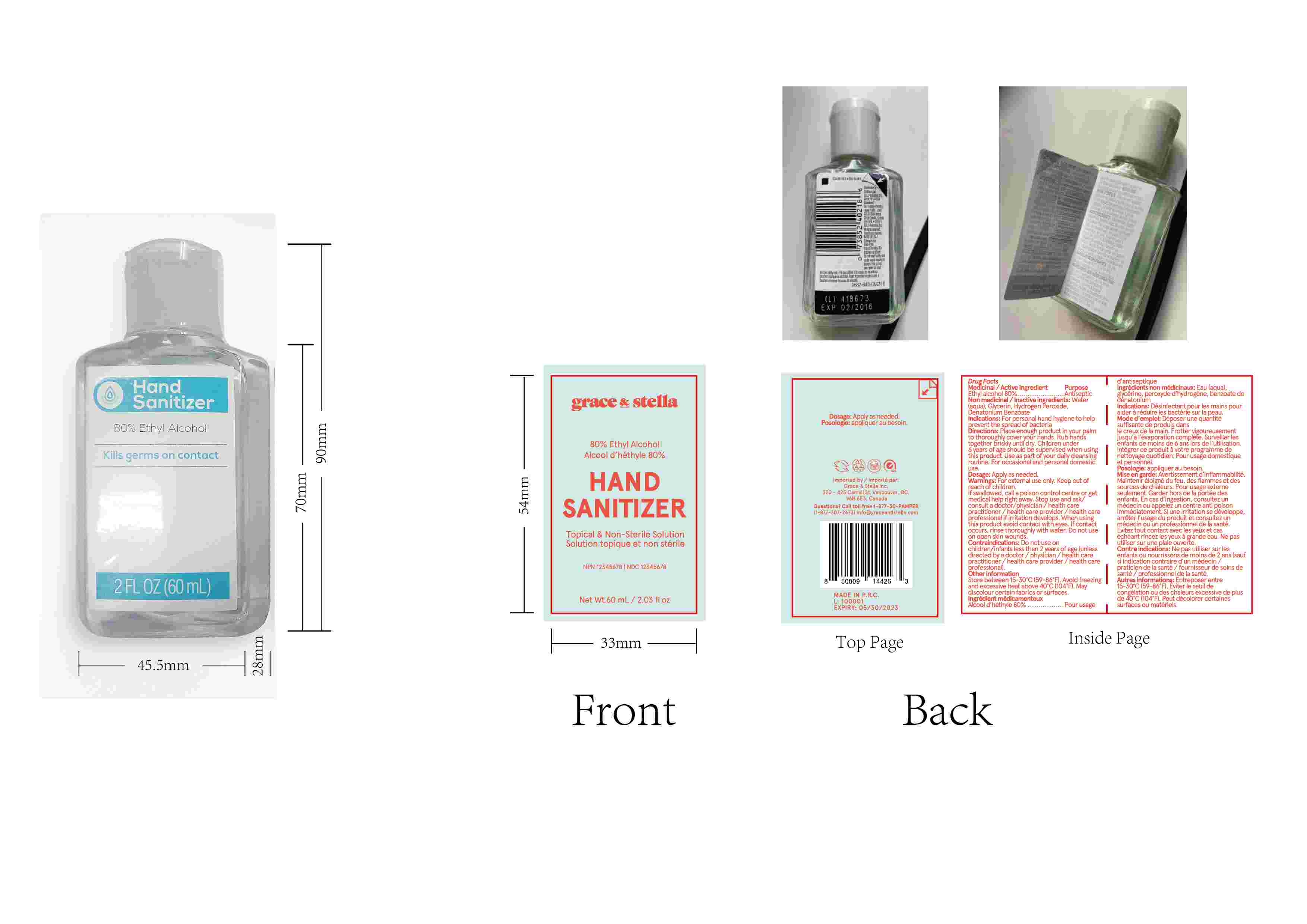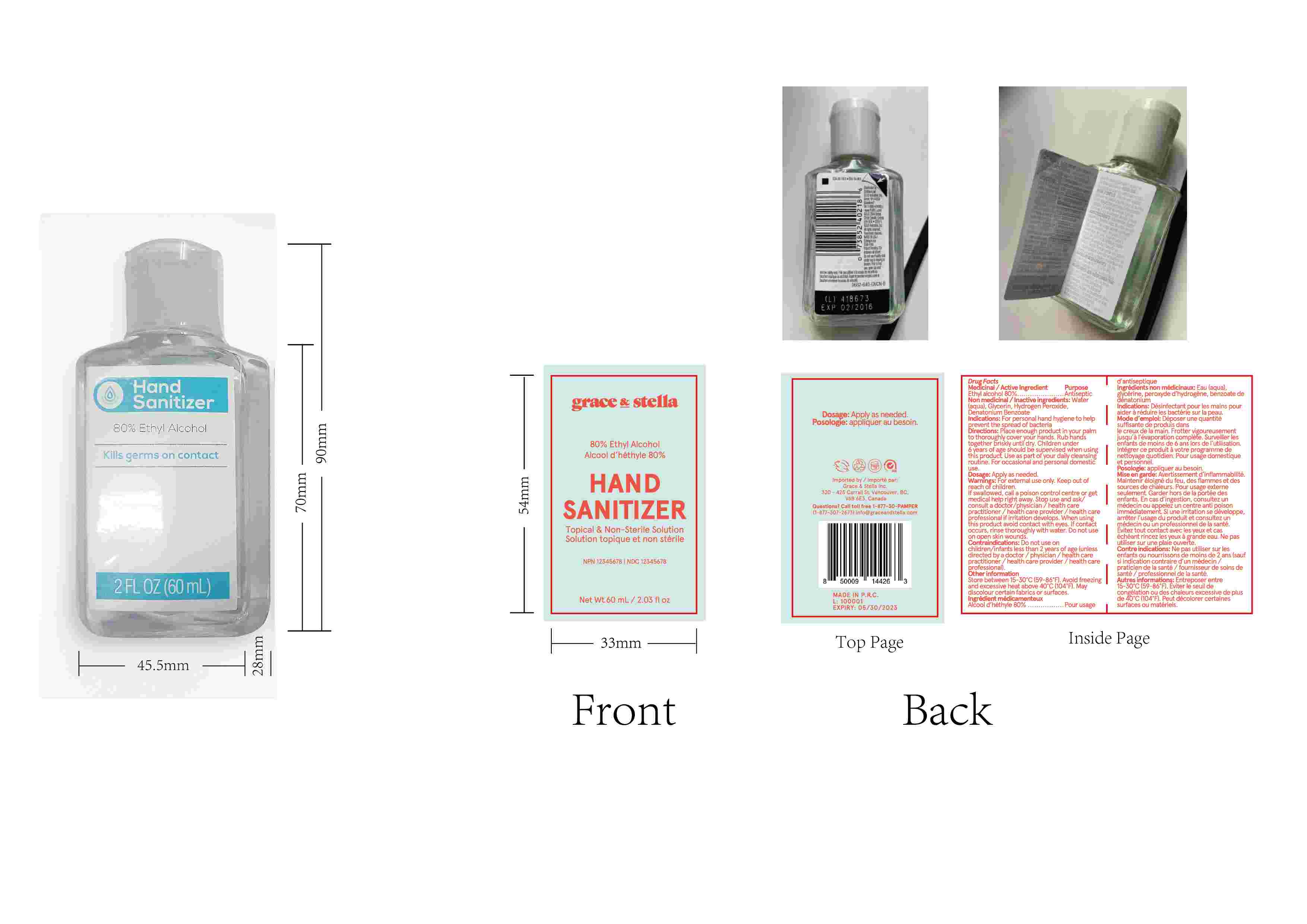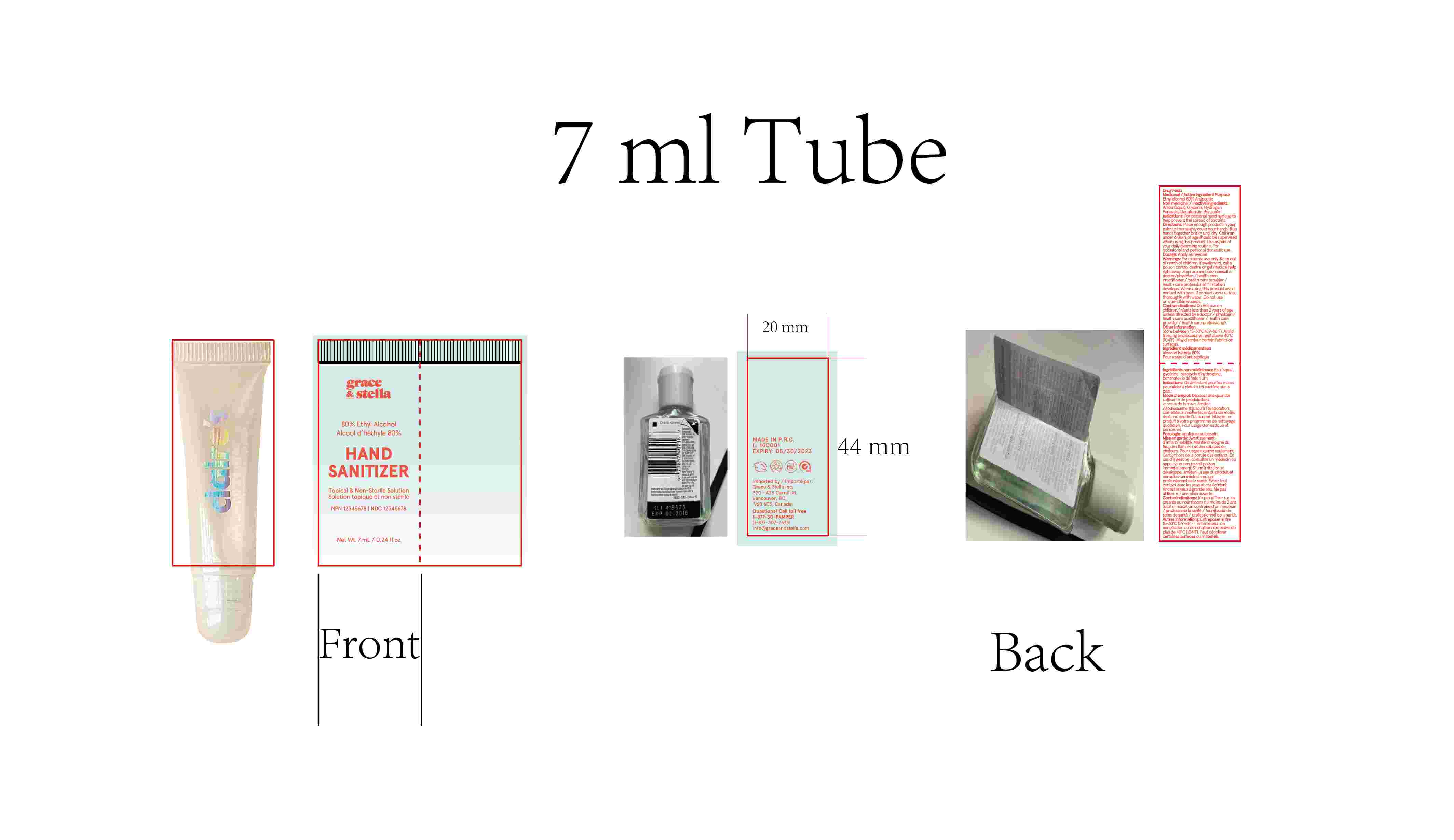 DRUG LABEL: Hand Sanitizer
NDC: 74862-002 | Form: LIQUID
Manufacturer: Yiwu Shining Cosmetics Co., Ltd.
Category: otc | Type: HUMAN OTC DRUG LABEL
Date: 20200623

ACTIVE INGREDIENTS: ALCOHOL 80 mL/100 mL
INACTIVE INGREDIENTS: HYDROGEN PEROXIDE; GLYCERIN; DENATONIUM BENZOATE; WATER

Hand Sanitizer

Active Ingredient(s)

Ethyl alcohol 80%

Purpose

Antiseptic

Use

For personal hand hygiene to help prevent the spread of bacteria

Warnings

For external use only. Keep out of reach of children. If swallowed, call a poison control centre or get medical help right away. Stop use and ask/ consult a doctor/physician I health care practitioner I health care provider I health care professional if irritation develops. When using this product avoid contact with eyes. If contact occurs, rinse thoroughly with water. Do not use
on open skin wounds.

Do not use on children/infants less than 2 years of age (unless directed by a doctor I physician I health care practitioner I health care provider I health care
professional).

When using this product avoid contact with eyes. If contact occurs, rinse thoroughly with water. Do not use on open skin wounds.

Stop use and ask/ consult a doctor/physician I health care practitioner I health care provider I health care professional if irritation develops.

Keep out of reach of children. If swallowed, call a poison control centre or get medical help right away.

Directions

Place enough product in your palm to thoroughly cover your hands. Rub hands together briskly until dry. Children under 6 years of age should be supervised when using this product Use as part of your daily cleansing routine. For occasional and personal domestic use.

Other information

Store between 15-30°C (59-86°F). Avoid freezing and excessive heat above 40°C (104°F). May discolour certain fabrics or surfaces.

Inactive ingredients

Water (aqua). Glycerin, Hydrogen Peroxide, Denatonium Benzoate